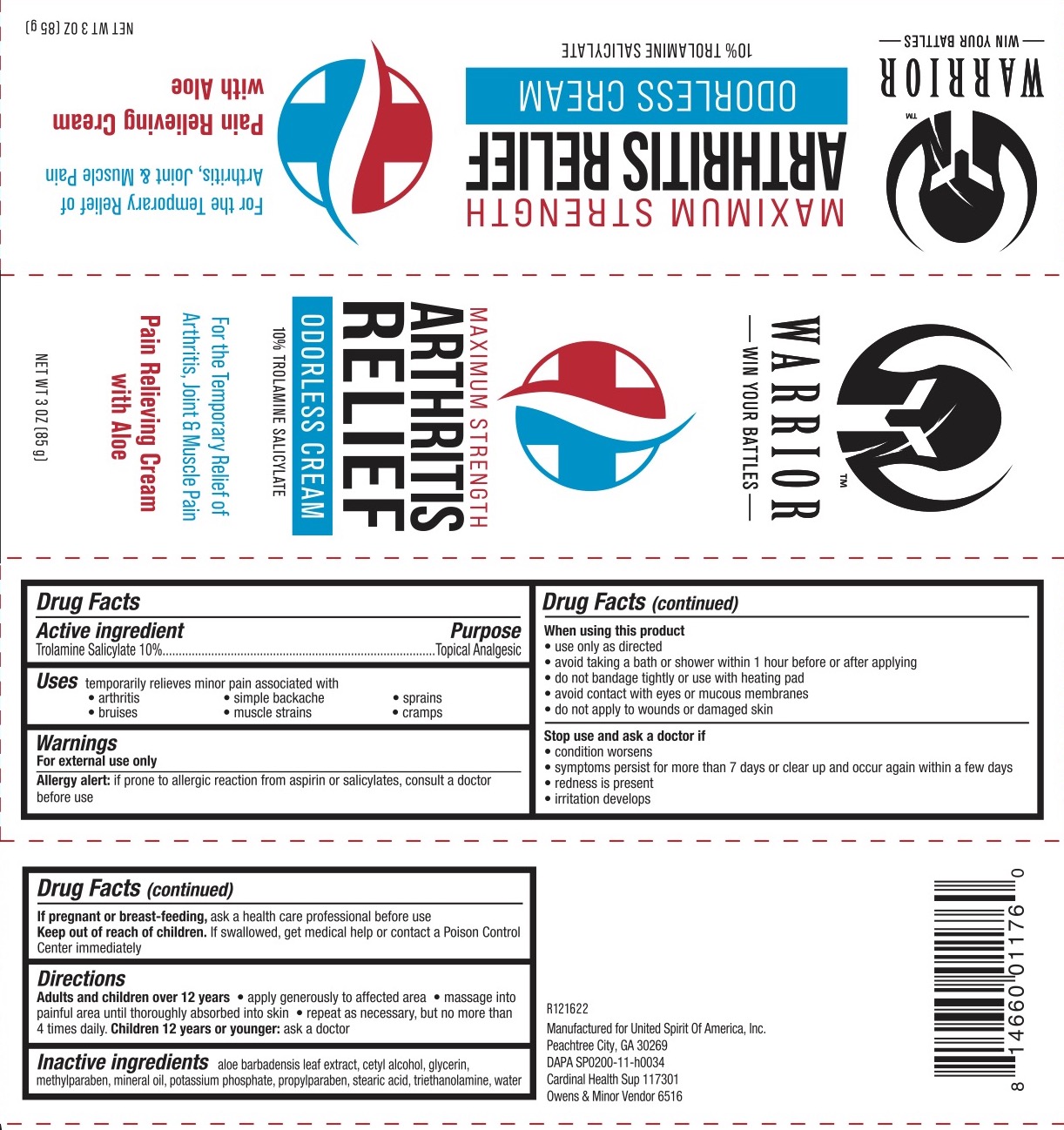 DRUG LABEL: Warrior Arthritis Relief
NDC: 72839-213 | Form: CREAM
Manufacturer: Derma Care Research Labs, LLC
Category: otc | Type: HUMAN OTC DRUG LABEL
Date: 20250127

ACTIVE INGREDIENTS: TROLAMINE SALICYLATE 10 g/100 g
INACTIVE INGREDIENTS: STEARIC ACID; CETYL ALCOHOL; WATER; GLYCERIN; TROLAMINE; METHYLPARABEN; MINERAL OIL; POTASSIUM PHOSPHATE, MONOBASIC; PROPYLPARABEN; ALOE VERA LEAF

Warrior Arthritis Relief, 10% Trolamine Salicylate

ACTIVE INGREDIENT

Trolamine Salicylate 10%

PURPOSE

Topical Analgesic.

DOSAGE AND ADMINISTRATION

Temporarily relieves minor pain associated with arthritis, simple backache, muscle strains, sprains, and cramps.

WARNINGS

For external use only.

Allergy Alert: if prone to allergic reaction from aspirin or salicylates, consult a doctor before use.

When using this product use only as directed, avoid taking a bath or shower within 1 hour before or after applying, do not bandage or use with a heating pad, avoid contact with eyes or mucous membranes, do not apply to wounds or damaged skin.

Stop use and ask a doctor if condition worsens or symptoms persist for more than 7 days, if symptoms clear up and occur again within a few days, or if irritation develops.

Keep out of reach of children.

PREGNANCY OR BREAST FEEDING

If pregnant or breast-feeding, ask a health care professional before use.

INDICATIONS AND USAGE

Adults and children 12 years of age: apply generously to the affected area, massage into painful area until thoroughly absorbed into the skin, repeat as necessary, but not more than 3 to 4 times daily. Children under 12 years of age: ask a doctor.

INACTIVE INGREDIENT

Aloe Barbadensis Leaf Juice, Cetyl Alcohol, Glycerin, Methylparaben, Mineral Oil, Potassium Phosphate, Propylparaben, Stearic Acid, Triethanolamine, Water.